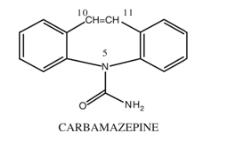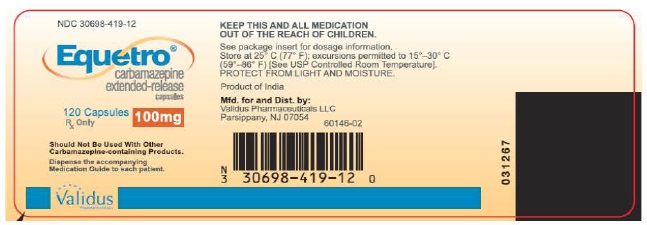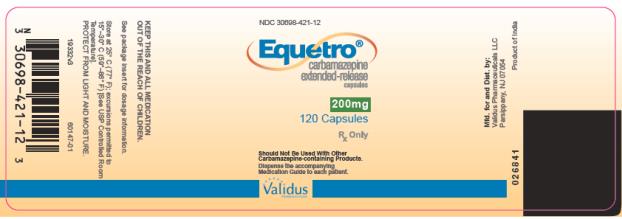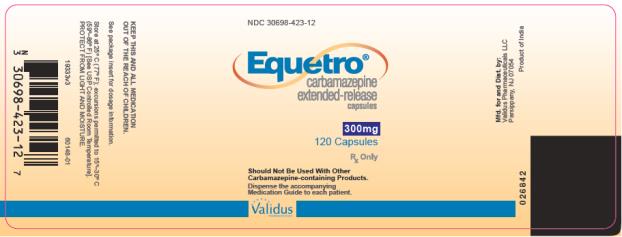 DRUG LABEL: EQUETRO
NDC: 30698-419 | Form: CAPSULE, EXTENDED RELEASE
Manufacturer: Validus Pharmaceuticals LLC
Category: prescription | Type: HUMAN PRESCRIPTION DRUG LABEL
Date: 20250819

ACTIVE INGREDIENTS: CARBAMAZEPINE 100 mg/1 1
INACTIVE INGREDIENTS: CITRIC ACID MONOHYDRATE; SILICON DIOXIDE; LACTOSE MONOHYDRATE; MICROCRYSTALLINE CELLULOSE; POLYETHYLENE GLYCOL, UNSPECIFIED; POVIDONE; SODIUM LAURYL SULFATE; TALC; TRIETHYL CITRATE; GELATIN; FD&C BLUE NO. 2; FERRIC OXIDE YELLOW; TITANIUM DIOXIDE

HIGHLIGHTS OF PRESCRIBING INFORMATION

These highlights do not include all the information needed to use EQUETROn safely and effectively. See full prescribing information for EQUETRO.
EQUETRO (carbamazepine) extended-release capsules, for oral use
Initial U.S. Approval:1968

RECENT MAJOR CHANGES

Warnings and Precautions (5.5) 10/2022

WARNING:SERIOUS DERMATOLOGIC REACTIONS AND APLASTIC ANEMIA AND AGRANULOCYTOSIS

WARNING:SERIOUS DERMATOLOGIC REACTIONSAND APLASTIC ANEMIA AND AGRANULOCYTOSIS

See full prescribing information for complete boxed warning.

Serious Dermatologic Reactions

• Serious and sometimes fatal dermatologic reactions, including toxic epidermal necrolysis (TEN) and Stevens-Johnson Syndrome (SJS), have occurred with EQUETRO (5.1)

• Patients of Asian ancestry have a 10-fold greater risk of TEN/SJS, compared to other populations. In genetically at-risk patients, test for the HLA-B*1502 allele prior to initiating EQUETRO (2.1, 5.1)

• Discontinue EQUETRO if these reactions occur (5.1)

Aplastic Anemia and Agranulocytosis

• Aplastic anemia and agranulocytosis occurred with EQUETRO (5.2)

• Obtain complete pretreatment hematological testing. Consider discontinuing EQUETRO if significant bone marrow depression develops (2.1, 5.2)

1INDICATIONS AND USAGE

EQUETRO is:

- A mood stabilizer indicated for the treatment of acute manic or mixed episodes associated with bipolar I disorder (1.1)
- Indicated for the treatment of the pain associated with trigeminal neuralgia (1.2)
- An anti-epileptic drug (AED) indicated for the treatment of partial seizures with complex symptomatology, generalized tonic-clonic seizures, and mixed seizures (1.3)

2 DOSAGE AND ADMINISTRATION

- SEE DOSAGE FOR BIPOLAR DISORDER, TRIGEMINAL NEURALGIA, AND EPILEPSY (2.2, 2.3, 2.4)
- When discontinuing treatment, reduce dose gradually (2.6, 5.6)
- Monitoring serum carbamazepine concentrations may be useful in dose selection and minimizing risk of toxicity (2.7)
- Swallow capsules whole or open capsules and sprinkle beads over food (2.8)
- Do not crush or chew the capsule or beads (2.8)

3 DOSAGE FORMS AND STRENGTHS

Extended-Release Capsules: 100 mg, 200 mg, and 300 mg (3)

4 CONTRAINDICATIONS

- Bone marrow depression (4)
- Known hypersensitivity to carbamazepine (4)
- Known hypersensitivity to tricyclic antidepressants (4)
- Concomitant use with monoamine oxidase inhibitors (MAOIs) or use within 14 days of discontinuing an MAOI (4)
- Concomitant use with delavirdine or other non-nucleoside reverse transcriptase inhibitors that are substrates for CYP3A4. EQUETRO decreases efficacy of these drugs (4, 5.9)
- Concomitant use of nefazodone (4)

5 WARNINGS AND PRECAUTIONS

- Drug Reaction with Eosinophilia and Systemic Symptoms:Monitor for hypersensitivity. Discontinue if another cause can not be established (5.3)
- Suicidal Behavior and Ideation: Monitor for depression, suicidal thoughts or behavior, and/or any unusual changes in mood or behavior (5.4)
- Embryofetal Toxicity: Advise women of child-bearing potential of possible risks to the fetus (5.5, 8.1, 8.3)
- Abrupt Discontinuation and Risk of Seizure: Taper the dose when discontinuing treatment (5.6).
- Hyponatremia: Consider discontinuing EQUETRO in patients with significant symptomatic hyponatremia (5.7).
- Cognitive and Motor Impairment: Advise patients not to drive or operate machinery until they have gained sufficient experience on EQUETRO to gauge whether it adversely affects these activities (5.8).
- Liver Damage:Monitor liver function. Discontinue EQUETRO with aggravated liver dysfunction or active liver disease (5.10).
- Hepatic Porphyria: Avoid EQUETRO use in patients with hepatic porphyria: can cause acute episodes of porphyria (5.12)

6 ADVERSE REACTIONS

Most common (>5% and 2 times placebo) adverse reactions were dizziness, somnolence, nausea, vomiting, ataxia, constipation, pruritus, dry mouth, asthenia, blurred vision, and speech disorder (6.1)

To report SUSPECTED ADVERSE REACTIONS, contact Validus Pharmaceuticals LLC at 1-866-982-5438 or FDA at 1-800-FDA-1088 or www.fda.gov/medwatch.

7 DRUG INTERACTIONS

- Cytochrome (CYP) 3A4 inhibitors, epoxide hydrolase inhibitors, CYP3A4 inducers, drugs metabolized by CYP1A2 or CYP3A4 (oral contraceptives, delavirdine, nefazodone), phenytoin, CNS depressants, lithium, chloroquine, mefloquine (7.1, 7.2, 7.3)
- Equetro may decrease the effectiveness of hormonal contraceptives. Use alternative form of birth control (7.2)

8 USE IN SPECIFIC POPULATIONS

Pregnancy: Can cause fetal harm. (5.5, 8.1)

Infertility: May impair male fertility (8.3)

FULL PRESCRIBING INFORMATION

WARNING:SERIOUS DERMATOLOGIC REACTIONS AND APLASTIC ANEMIA AND AGRANULOCYTOSIS

Serious Dermatologic Reactions and HLA-B*1502 Allele

Serious and sometimes fatal dermatologic reactions, including toxic epidermal necrolysis (TEN) and Stevens-Johnson Syndrome (SJS), have occurredb in patients treated with carbamazepine. These syndromes may be accompanied by mucous membrane ulcers, fever, or painful rash. These reactions are estimated to occur in 1 to 6 per 10,000 new users in countries with mainly Caucasian populations, but the risk in patients of Asian descent is estimated to be about 10 times higher. There is a strong association between the risk of developing SJS/TEN and the presence of HLA-B*1502, an inherited allelic variant of the HLA-B gene. Test for HLA-B*1502, prior to initiating EQUETROin patients with an increased likelihood of carrying this allele. Avoid use of EQUETRO in patients testing positive for the allele unless the benefit clearly outweighs the risk. Discontinue EQUETRO if you suspect that the patient has a serious dermatologic reaction [see Warnings and Precautions (5.1)].

Aplastic Anemia and Agranulocytosis

Aplastic anemia and agranulocytosis can occurduring treatment with EQUETRO. The risk of developing these reactions with EQUETRO is 5-8 times greater than in the general population. However, the overall risk in the general population is low (6 cases in a population of one million per year for agranulocytosis and two cases in a population of one million per year for aplastic anemia). Obtain a complete blood count before beginning treatment with EQUETRO, and monitor CBC periodically.

Consider discontinuing EQUETRO if significant bone marrow depression develops [see Warnings and Precautions (5.2) ].

1INDICATIONS AND USAGE

1.1Acute Manic or Mixed Episodes associated with Bipolar I Disorder

EQUETRO is indicated for treatment of patients with acute manic or mixed episodes associated with bipolar I disorder [see Clinical Studies (14.1)].

1.2 Pain of Trigeminal Neuralgia

EQUETRO is indicated in the treatment of the pain associated with trigeminal neuralgia. Beneficial results have also been reported in glossopharyngeal neuralgia. This drug is not a simple analgesic and should not be used for the relief of trivial aches or pains.

1.3 Epilepsy

EQUETRO is indicated for the treatment of partial seizures with complex symptomatology (e.g., psychomotor, temporal lobe), generalized tonic-clonic seizures (grand mal), and mixed seizure patterns, which include the seizure types listed here or other partial or generalized seizures.

Limitations of Usage

EQUETRO is not indicated for the treatment of absence seizures (petit mal).Carbamazepine has been associated with increased frequency of generalized convulsions in these patients.

2 DOSAGE AND ADMINISTRATION

2.1 Pretreatment Screening

Prior to initiating treatment with EQUETRO, test patients with ancestry in genetically at-risk populations for the presence of the HLA-B*1502 allele. The high resolution genotype test is positive if one or two HLA-B*1502 alleles are present. Avoid use of EQUETRO in patients testing positive for the allele, unless the benefit clearly outweighs the risk [see Boxed Warning, Warnings and Precautions (5.1)].

Complete pretreatment blood counts, including platelets and possibly reticulocytes and serum iron, should be obtained as a baseline. If a patient in the course of treatment exhibits low or decreased white blood cell or platelet counts, the patient should be monitored closely. Discontinuation of EQUETRO should be considered if any evidence of significant bone marrow depression develops [see Warnings and Precautions (5.2)].

Baseline and periodic evaluations of liver function, particularly in patients with a history of liver disease, must be performed during treatment with EQUETRO because liver damage may occur. Discontinue EQUETRO in cases of aggravated liver dysfunction or active liver disease [see Warnings and Precautions (5.10)].

Baseline and periodic eye examinations, including slit-lamp, funduscopy, and tonometry, are recommended since many phenothiazines and related drugs have been shown to cause eye changes [see Warnings and Precautions (5.13)].

Baseline and periodic complete urinalysis and BUN determinations are recommended for patients treated with this agent because of observed renal dysfunction.

2.2 Dosage for Acute Manic or Mixed Episodes Associated with Bipolar I Disorder

The recommended initial dose of EQUETRO is 200 mg administered twice daily. The dose may be increased by 200 mg per day to achieve optimal clinical response. Doses higher than 1600 mg per day have not been studied in mania associated with bipolar disorder.

2.3 Dosage for Pain of Trigeminal Neuralgia

Initial: On the first day, start with one 200 mg capsule once daily. This dose may be increased by up to 200 mg/day using increments of 100 mg every 12 hours only as needed to reach an effective and tolerated dose. Do not exceed a total daily dose of 1200 mg.

Maintenance: Control of pain can be maintained in most patients with 400 mg to 800 mg daily. However, some patients may be maintained on as little as 200 mg daily, while others may require as much as 1200 mg daily. At least once every 3 months throughout the treatment period, attempts should be made to reduce the dose to the minimum effective level or even to discontinue the drug.

2.4 Dosage for Epilepsy

Adults and Children over 12 Years of Age

The recommended initial dose is 200 mg administered twice daily. Increase in weekly increments of 200 mg a day, administered as an equally divided, twice daily dose, until an optimal response is obtained. Dosage generally should not exceed 500 mg twice daily in children 12 to 15 years old; 600 mg twice daily in children 15 to 18 years old; and 800 mg twice daily in adults.

Children Under 12 Years of Age

Ordinarily, optimal clinical response is achieved at daily doses below 35 mg/kg [see Dosage and Administration (2.5)]. No recommendation regarding the safety of EQUETRO for use at doses above 35 mg/kg/24 hours can be made.

Co-Administration with Other AEDs

EQUETRO may be used alone or with other AEDs. When added to existing AEDs, add EQUETRO gradually while the dosage(s) of other AEDs are maintained or gradually decreased. Potential drug interactions should be considered when using carbamazepine with other AEDs [see Drug Interactions (7.1,7.2)].

2.5 Switching from Immediate-Release Carbamazepine to EQUETRO

EQUETRO is an extended-release formulation for twice a day administration. When converting patients from immediate release carbamazepine to EQUETRO extended-release capsules, the same total daily mg dose of carbamazepine should be administered. Following conversion to EQUETRO, patients should be closely monitored for seizure control. Depending on the therapeutic response after conversion, the total daily dose may need to be adjusted within the recommended dosing instructions.

2.6 Discontinuation of EQUETRO

When discontinuing EQUETRO used for any indication, reduce the dose gradually and avoid abrupt discontinuation in order to decrease the risk of seizure [see Warnings and Precautions (5.6)].

2.7 Monitoring Serum Carbamazepine Concentration

Monitoring serum carbamazepine concentrations may be useful for dose selection, minimizing toxicity, and verifying drug compliance, especially in clinical conditions in which alterations in EQUETRO metabolism can occur (e.g., drug interactions) [see Drug Interactions (7)]. In pediatric patients treated with EQUETRO for epilepsy, if satisfactory clinical response has not been achieved, measure plasma levels to determine whether or not they are in the therapeutic range.

2.8 Administration Instructions

Swallow EQUETRO capsules whole or open and sprinkle the beads over food, such as a teaspoon of applesauce. Do not crush or chew EQUETRO capsules or the beads inside the capsule. EQUETRO can be taken with or without meals.

3 DOSAGE FORMS AND STRENGTHS

EQUETRO (carbamazepine) extended-release capsules for oral administration is supplied in three dosage strengths:

- 100 mg — Two-piece hard gelatin capsule yellow opaque cap with bluish green opaque body printed with SPD417 on one end and SPD417 and 100 mg on the other in white ink.
- 200 mg — Two-piece hard gelatin capsule yellow opaque cap with blue opaque body printed with SPD417 on one end and SPD417 and 200 mg on the other in white ink.
- 300 mg — Two-piece hard gelatin capsule yellow opaque cap with blue body printed with SPD417 on one end and SPD417 and 300 mg on the other in white ink.

4 CONTRAINDICATIONS

- Bone marrow depression [see Warnings and Precautions (5.2)].
- Known hypersensitivity to carbamazepine, such as anaphylaxis or serious hypersensitivity reaction [see Warnings and Precautions (5.3)].
- Known hypersensitivity to any of the tricyclic compounds (e.g., amitriptyline, desipramine, imipramine, protriptyline, and nortriptyline.) Hypersensitivity reactions include anaphylaxis and serious rash.
- Concomitant use of delavirdine or other non-nucleoside reverse transcriptase inhibitors that are substrates for CYP3A4. EQUETRO can substantially reduce the concentrations of these drugs through induction of CYP3A4. This can lead to loss of virologic response and possible resistance to these medications [see Warnings and Precautions (5.9) and Drug Interactions (7.2)].
- Concomitant use of monoamine oxidase inhibitors (MAOIs). Before beginning treatment with EQUETRO, MAOIs should be discontinued for a minimum of 14 days. Concomitant use can cause serotonin syndrome.
- Concomitant use of nefazodone. This may result in insufficient plasma concentrations of nefazodone and its active metabolite to achieve a therapeutic effect.

5 WARNINGS AND PRECAUTIONS

5.1 Serious Dermatologic Reactions

Serious and sometimes fatal dermatologic reactions, including toxic epidermal necrolysis (TEN) and Stevens-Johnson syndrome (SJS), have been reported with carbamazepine treatment. These syndromes may be accompanied by mucous membrane ulcers, fever, or painful rash. Over 90% of carbamazepine-treated patients who experienced SJS/TEN developed these reactions within the first few months of treatment. The risk of these reactions is estimated to be about 1 to 6 per 10,000 new users in countries with mainly Caucasian populations. However, the risk in some Asian countries is estimated to be about 10 times higher. Discontinue EQUETRO if you suspect that the patient has a serious dermatologic reaction. If signs or symptoms suggest SJS/TEN, do not resume treatment with EQUETRO.

SJS, TEN, and HLA-B*1502 Allele

Retrospective case-control studies have found that in patients of Chinese ancestry there is a strong association between the risk of developing SJS/TEN with EQUETRO treatment and the presence of the HLA-B*1502 allele (an inherited variant of the HLA-B gene). Prior to initiating EQUETRO therapy in patients at higher likelihood for this allele, perform testing for HLA-B*1502. The high resolution genotype test is positive if one or two HLA-B*1502 alleles are present. Avoid use of EQUETRO in patients positive for the HLA-B*1502 allele unless the benefits clearly outweighs the risks of serious dermatologic reactions. Tested patients who are found to be negative for the allele are thought to have a low risk of SJS/TEN associated with carbamazepine treatment.

The prevalence of the HLA-B*1502 allele may be higher in Asian populations: Hong Kong, Thailand, Malaysia, and parts of the Philippines (greater than 15%); Taiwan (10%), North China (4%); south Asians, including Indians (2 to 4%); and Japan and Korea (less than 1%). HLA-B*1502 is largely absent in individuals not of Asian origin (e.g., Caucasians, African-Americans, Hispanics, and Native Americans). The accuracy of estimated rates of the HLA-B*1502 allele in these populations may be limited by wide variability in rates within ethnic groups, the difficulty in ascertaining ethnic ancestry, and the likelihood of mixed ancestry.

The HLA-B*1502 allele has not been found to predict risk of less severe adverse cutaneous reactions from carbamazepine, such as maculopapular eruption (MPE) or to predict Drug Reaction with Eosinophilia and Systemic Symptoms (DRESS) [see Warnings and Precautions (5.3)].

Limited evidence suggests that HLA-B*1502 may be a risk factor for the development of SJS/TEN in patients of Chinese ancestry taking other anti-epileptic drugs associated with SJS/TEN, including phenytoin. Consideration should be given to avoiding use of other drugs associated with SJS/TEN in HLA-B*1502 positive patients, when alternative therapies are otherwise equally acceptable [see Dosage and Administration (2.1)].

Hypersensitivity Reactions and HLA-A*3101 Allele

Retrospective case-control studies in patients of European, Korean, and Japanese ancestry have found a moderate association between the risk of developing hypersensitivity reactions and the presence of HLA-A*3101, an inherited allelic variant of the HLA-A gene, in patients using carbamazepine. These hypersensitivity reactions include SJS/TEN, maculopapular eruptions, and Drug Reaction with Eosinophilia and Systemic Symptoms [see Warnings and Precautions (5.3)].

HLA-A*3101 is expected to be present in the following frequencies: greater than 15% in patients of Japanese, Native American, Southern Indian (for example, Tamil Nadu) and some Arabic ancestry; up to about 10% in patients of Han Chinese, Korean, European, Latin American, and other Indian ancestry; and up to about 5% in African-Americans and patients of Thai, Taiwanese, and Chinese (Hong Kong) ancestry.

The risks and benefits of EQUETRO therapy should be weighed before considering EQUETRO in patients known to be positive for HLA-A*3101.

Hypersensitivity and Limitations of HLA Genotyping

Application of HLA genotyping as a screening tool has important limitations and must never substitute for appropriate clinical vigilance and patient management. Many HLA-B*1502-positive and HLA-A*3101- positive patients treated with EQUETRO will not develop SJS/TEN or other hypersensitivity reactions, and these reactions can still occur infrequently in HLA-B*1502-negative and HLA-A*3101-negative patients of any ethnicity. The role of other possible factors in the development of, and morbidity from, SJS/TEN and other hypersensitivity reactions, such as AED dose, compliance, concomitant medications, co-morbidities, and the level of dermatologic monitoring have not been studied.

5.2 Aplastic Anemia and Agranulocytosis

Aplastic anemia and agranulocytosis have occurred in patients treated with carbamazepine. Data from a population-based case-control study suggest that the risk of developing these reactions is 5-8 times greater than in the general population. However, the overall risk of these reactions in the untreated general population is low, approximately six patients per one million population per year for agranulocytosis and two patients per one million population per year for aplastic anemia.

Although reports of transient or persistent decreased platelet or white blood cell counts are not uncommon in association with the use of carbamazepine, data are not available to estimate accurately their incidence or outcome. However, the vast majority of the cases of leukopenia have not progressed to the more serious conditions of aplastic anemia or agranulocytosis.

Because of the very low incidence of agranulocytosis and aplastic anemia, the vast majority of minor hematologic changes observed in monitoring of patients on EQUETRO are unlikely to signal the occurrence of either abnormality. Nonetheless, complete pretreatment hematological testing should be obtained as a baseline. If a patient in the course of treatment exhibits low or decreased white blood cell or platelet counts, the patient should be monitored closely. Consider discontinuing EQUETRO if any evidence of significant bone marrow depression develops. Clinical features can include fever, dyspnea on exertion, fatigue, easy bruising, petechiae, epistaxis, gingival bleeding, and heavy menses.

5.3 Drug Reaction with Eosinophilia and Systemic Symptoms/Multiorgan Hypersensitivity

Drug Reaction with Eosinophilia and Systemic Symptoms (DRESS), also known as Multiorgan Hypersensitivity, have occurred with carbamazepine. Some of these events have been fatal or life-threatening. DRESS typically, although not exclusively, presents with fever, rash, lymphadenopathy, and/or facial swelling, in association with other organ system involvement, such as hepatitis, nephritis, hematologic abnormalities, myocarditis, or myositis sometimes resembling an acute viral infection. Eosinophilia is often present. This disorder is variable in its expression, and other organ systems not noted here may be involved. It is important to note that early manifestations of hypersensitivity (e.g., fever, lymphadenopathy) may be present even though rash is not evident. If such signs or symptoms are present, the patient should be evaluated immediately. EQUETRO should be discontinued if an alternative etiology for the signs or symptoms cannot be established.

Hypersensitivity

Hypersensitivity reactions to carbamazepine have been reported in patients who previously experienced this reaction to anticonvulsants including phenytoin, primidone, and phenobarbital. If such history is present, benefits and risks should be carefully considered, and, if EQUETRO is initiated, the signs and symptoms of hypersensitivity should be carefully monitored.

In patients who have exhibited hypersensitivity reactions to carbamazepine, approximately 25 to 30% may experience hypersensitivity reactions with oxcarbazepine.

5.4 Suicidal Behavior and Ideation

Antiepileptic drugs (AEDs), including EQUETRO, increase the risk of suicidal thoughts or behavior in patients taking these drugs for any indication. Patients treated with any AED for any indication should be monitored for the emergence or worsening of depression, suicidal thoughts or behavior, and/or any unusual changes in mood or behavior.

Pooled analyses of 199 placebo-controlled clinical trials (mono- and adjunctive therapy) of 11 different AEDs showed that patients randomized to one of the AEDs had approximately twice the risk (adjusted Relative Risk 1.8, 95% CI:1.2, 2.7) of suicidal thinking or behavior compared to patients randomized to placebo. In these trials, which had a median treatment duration of 12 weeks, the estimated incidence rate of suicidal behavior or ideation among 27,863 AED-treated patients was 0.43%, compared to 0.24% among 16,029 placebo-treated patients, representing an increase of approximately one case of suicidal thinking or behavior for every 530 patients treated. There were four suicides in drug-treated patients in the trials and none in placebo-treated patients, but the number is too small to allow any conclusion about drug effect on suicide.

The increased risk of suicidal thoughts or behavior with AEDs was observed as early as one week after starting drug treatment with AEDs and persisted for the duration of treatment assessed. Because most trials included in the analysis did not extend beyond 24 weeks, the risk of suicidal thoughts or behavior beyond 24 weeks could not be assessed.

The risk of suicidal thoughts or behavior was generally consistent among drugs in the data analyzed. The finding of increased risk with AEDs of varying mechanisms of action and across a range of indications suggests that the risk applies to all AEDs used for any indication. The risk did not vary substantially by age (5 to100 years) in the clinical trials analyzed. Table 1 presents the absolute and relative risk by indication for all evaluated AEDs.

Table 1. Risk of suicidal thoughts or behavior (reactions) for antiepileptic drugs by indication in the pooled analysis
 | Placebo | Antiepileptic Drugs
Indication | Reactions Per 1000 Patients | Reactions Per 1000 Patients | Relative Risk: Incidence of Reactions in AED Group/ Incidence of Reactions in Placebo Group | Risk Difference: Additional Drug Patients with Events Per 1000 Patients
Epilepsy Psychiatric Other Total | 1.0 5.7 1.0 2.4 | 3.4 8.5 1.8 4.3 | 3.5 1.5 1.9 1.8 | 2.4 2.9 0.9 1.9

The relative risk for suicidal thoughts or behavior was higher in clinical trials for epilepsy than in clinical trials for psychiatric or other conditions, but the absolute differences were similar for the epilepsy and psychiatric indications.

Anyone considering prescribing EQUETRO or any other AED must balance the risk of suicidal thought or behavior with the risk of untreated illness. Epilepsy and many other illnesses for which AEDs are prescribed are themselves associated with morbidity and mortality and an increased risk of suicidal thoughts and behavior. Should suicidal thoughts and behavior emerge during treatment, the prescriber needs to consider whether the emergence of these symptoms in any given patient may be related to the illness being treated.

Patients, their caregivers, and families should be informed that AEDs increase the risk of suicidal thoughts and behaviors and should be advised of the need to be alert for the emergence or worsening of the signs and symptoms of depression, any unusual changes in mood or behavior, or the emergence of suicidal thoughts, behavior, or thoughts about self-harm. Behaviors of concern should be reported immediately to healthcare providers.

5.5 Embryofetal Toxicity

EQUETRO can cause fetal harm when administered to a pregnantfemale. [see Use in Specific Populations (8.1)]. Pregnancy registries and epidemiological data suggest a potential association between the use of carbamazepine during pregnancy and major congenital malformations, including neural tube defects and malformations involving other body systems (e.g., craniofacial defects and cardiovascular malformations). These available data suggest that, compared with monotherapy, there may be a higher prevalence of teratogenic effects associated with the use of anticonvulsants in combination therapy.

In animal studies, administration of carbamazepine at clinically relevant doses during pregnancy resulted in developmental toxicity, including increased incidences of fetal malformations.

Inform females who may become pregnant about the potential increased risk of major congenital malformations with EQUETRO use during pregnancy. Assess the risks and benefits of EQUETRO and discuss with the patient to determine if an alternative treatment should be considered. EQUETRO can reduce the effectiveness of hormonal contraceptives. Females of reproductive potential should be counseled on the consistent use of effective nonhormonal contraception or barrier methods during treatment with EQUETRO [see Drug Interactions (7.2) and Use in Specific Populations (8.1,8.3)].

5.6 Abrupt Discontinuation and Risk of Seizure

Do not discontinue EQUETRO abruptly, because of the risk of seizure and other withdrawal signs/symptoms. Patients with seizure disorder are at increased risk of developing seizure and status epilepticus with attendant hypoxia and threat to life. However, in the event of an allergic or hypersensitivity reaction, more rapid substitution of alternative therapy may be necessary.

5.7 Hyponatremia

Hyponatremia can occur as a result of treatment with EQUETRO. In many cases, the hyponatremia appears to be caused by the syndrome of inappropriate antidiuretic hormone secretion (SIADH). The risk of developing SIADH with EQUETRO treatment appears to be dose-related. Elderly patients and patients treated with diuretics are at greater risk of developing hyponatremia. Signs and symptoms of hyponatremia include headache, new or increased seizure frequency, difficulty concentrating, memory impairment, confusion, weakness, and unsteadiness, which can lead to falls. Consider discontinuing EQUETRO in patients with symptomatic hyponatremia.

5.8 Potential for Cognitive and Motor Impairment

EQUETRO has the potential to cause impairment in judgment, cognition, and motor function. Caution patients about operating hazardous machinery, including automobiles, until they are reasonably certain the EQUETRO does not affect them adversely .Adverse reactions in the clinical trials in bipolar disorder included (EQUETRO, N= 251 and Placebo, N= 248): somnolence (32% vs. 13%), ataxia (15% vs. 0.4%), dizziness (44% vs. 12%), vertigo (2% vs. 1%), thinking abnormal (2% vs. 0.4%), tremor (3% vs. 1%), and blurred vision (6% vs. 2%) [see Adverse Reactions (6.1)].

5.9 Potential for Loss of Virologic Response to Non-nucleoside Reverse Transcriptase Inhibitorsthat are substrates for CYP3A4 with Concomitant Use of EQUETRO

Coadministration of EQUETRO with non-nucleoside reverse transcriptase inhibitors, including delavirdine, is contraindicated because it may lead to loss of virologic response and possible resistance. Through induction of CYP3A4, EQUETRO can markedly decrease the concentrations of these drugs. Coadministration of delavirdine, an NNRTI and a substrate of CYP3A4, and EQUETRO can decrease delavirdine concentrations by 90% [see Contraindications (4), Drug Interactions (7.2)].

5.10 Liver Damage

Hepatic effects, ranging from slight elevations in liver enzymes to rare cases of hepatic failure have been reported. In some cases, hepatic effects may progress despite discontinuation of the drug. In addition rare instances of vanishing bile duct syndrome have been reported. This syndrome consists of a cholestatic process with a variable clinical course ranging from fulminant to indolent, involving the destruction and disappearance of the intrahepatic bile ducts. Some, but not all, cases are associated with features that overlap with other immunoallergenic syndromes such as serious dermatologic reactions and Drug Reaction with Eosinophilia and Systemic Symptoms/Multiorgan Hypersensitivity [see Warnings and Precautions (5.1,5.2)].

Baseline and periodic evaluations of liver function, particularly in patients with a history of liver disease, must be performed during treatment with this drug since liver damage may occur. The drug should be discontinued immediately in cases of aggravated liver dysfunction or active liver disease.

5.11 AV Heart Block

AV heart block, including second and third degree block, have been reported following carbamazepine treatment. This occurred generally, but not solely, in patients with underlying EKG abnormalities or risk factors for conduction disturbances.

5.12 Hepatic Porphyria

The use of EQUETRO should be avoided in patients with a history of hepatic porphyria (e.g., acute intermittent porphyria, variegate porphyria, porphyria cutanea tarda). Acute attacks have been reported in such patients receiving carbamazepine therapy. EQUETRO administration has also been demonstrated to increase porphyrin precursors in rodents, a presumed mechanism for the induction of acute attacks of porphyria.

5.13 Increased Intraocular Pressure

Carbamazepine has mild anticholinergic activity. In patients with a history of increased intraocular pressure, consider assessing intraocular pressure before initiating treatment and periodically during therapy.

6 ADVERSE REACTIONS

The following serious adverse reactions are discussed in more detail in other sections of the labeling:

- Serious Dermatologic Reactions: Toxic Epidermal Necrolysis and Stevens-Johnson Syndrome [see Warnings and Precautions (5.1)
- Aplastic anemia/agranulocytosis [see Warnings and Precautions (5.2)]
- Drug Reaction with Eosinophilia and Systemic Symptoms/Multiorgan Hypersensitivity [see Warnings and Precautions (5.3)]
- Suicidal Behavior and Ideation [see Warnings and Precautions (5.4)]
- Embryofetal Toxicity [see Warnings and Precautions (5.5)]
- Abrupt Discontinuation and Seizure Risk [see Warnings and Precautions (5.6)]
- Hyponatremia [see Warnings and Precautions (5.7)]
- Cognitive and Motor Impairment [see Warnings and Precautions (5.8)]
- Drug Interaction with Non-Nucleoside Reverse Transcriptase Inhibitors [see Warnings and Precautions (5.9)]
- Liver Damage [see Warnings and Precautions (5.10)]
- AV Heart Block [see Warnings and Precautions (5.11)]
- Hepatic Porphyria [see Warnings and Precautions (5.12)]
- Increased Intraocular Pressure [see Warnings and Precautions (5.13)]

6.1 Clinical Trials Experience

Because clinical trials are conducted under widely varying conditions, adverse reaction rates observed in the clinical trials of a drug cannot be directly compared to rates in the clinical trials of another drug and may not reflect the rates observed in clinical practice.

The most commonly reported adverse reactions (>5% in the EQUETRO group and at least twice placebo) in the pooled 3-week placebo-controlled trials in patients with acute mania associated with Bipolar I Disorder (Studies 1 and 2) were dizziness, somnolence, nausea, vomiting, ataxia, constipation, pruritus, dry mouth, asthenia, blurred vision, and speech disorder [see Clinical Studies (14.1)]. The EQUETRO doses used were 400 to 1600 mg per day.

(Incidence > 2% and greater than placebo)
Adverse Reactions | EQUETRO® (N = 251) | Placebo (N = 248)
Dizziness | 44% | 12%
Somnolence | 32% | 13%
Nausea | 29% | 10%
Vomiting | 18% | 3%
Ataxia | 15% | 0.4%
Constipation | 10% | 5%
Pruritus | 8% | 2%
Dry Mouth | 8% | 3%
Asthenia | 8% | 4%
Rash | 7% | 4%
Blurred vision | 6% | 2%
Speech Disorder | 6% | 0.4%
Hypertension | 3% | 0.4%
Paresthesia | 2% | 1%
Thinking abnormal | 2% | 0.4%
Tremor | 3% | 1%
Twitching | 2% | 1%
Vertigo | 2% | 1%

6.2 Postmarketing Experience

The following adverse reactions have been identified during post approval use of EQUETRO. Because these reactions are reported voluntarily from a population of uncertain size, it is not always possible to reliably estimate their frequency or establish a causal relationship to drug exposure.

Nervous System:confusion, diplopia, oculomotor disturbances, nystagmus, speech disturbances, abnormal involuntary movements, tinnitus.

Digestive System:gastric distress, abdominal pain, diarrhea, anorexia.

Laboratory Tests: thyroid function tests (T3, T4)- decreased values

Other:lupus erythematosus-like syndrome

One case of aseptic meningitis, accompanied by myoclonus and peripheral eosinophilia, has been reported in a patient taking carbamazepine in combination with other medications. The patient was successfully dechallenged, and the meningitis reappeared upon rechallenge with carbamazepine.

6.3 Additional Adverse Reactions Associated with Carbamazepine

The following is a list of additional adverse reactions identified in clinical trials or postmarketing reports of other forms of carbamazepine and not reported above for EQUETRO. Because these reactions were reported voluntarily from a population of uncertain size, it is not always possible to estimate their frequency reliably or to establish a causal relationship to drug exposure.

Nervous System:Isolated cases of neuroleptic malignant syndrome have been reported in carbamazepine use both with and without concomitant use of other psychotropic drugs.

Skin:onychomadesis, acute generalized exanthematous pustulosis (AGEP).

To report SUSPECTED ADVERSE REACTIONS, contact Validus Pharmaceuticals LLC at 1-866-982-5438 or FDA at 1-800-FDA-1088 orwww.fda.gov/medwatch.

7 DRUG INTERACTIONS

7.1 Pharmacokinetic Effectsof other Drugs on EQUETRO

Drugs that Inhibit Cytochrome P450 3A4 (CYP3A4)

EQUETRO is metabolized primarily by CYP3A4 to the active carbamazepine-10,11-epoxide, which is further metabolized to the trans-diol by epoxide hydrolase. Inhibitors of CYP 3A4 and/or epoxide hydrolase can increase plasma levels of EQUETRO and its active metabolites, increasing plasma concentrations of EQUETRO and the risk of adverse reactions. It may be necessary to reduce the EQUETRO dose if used concomitantly with inhibitors of CYP3A4 and/or epoxide hydrolase. The following drugs are CYP3A4 inhibitors:

Acetazolamide, aprepitant, azole antifungals (e.g., ketoconazole, itraconazole, fluconazole, voriconazole), cimetidine, ciprofloxacin, clarithromycin, dalfopristin, danazol, dantrolene, delavirdine, diltiazem, erythromycin, fluoxetine, fluvoxamine, grapefruit juice, ibuprofen, isoniazid, loratadine, nefazodone, niacinamide, nicotinamide, olanzapine, omeprazole, oxybutynin, quinine, quinupristin, ticlopidine, troleandomycin, valproate, verapamil, zileuton.

Drugs that Inhibit Epoxide Hydrolaseand CYP3A4

Clarithromycin, erythromycin, loxapine, quetiapine, and valproate also inhibit epoxide hydrolase, resulting in increased levels of the active metabolite carbamazepine-10,11-epoxide [see Clinical Pharmacology (12.3)].

Drugs that Induce CYP3A4

CYP3A4 inducers can decrease serum concentrations of EQUETRO and decrease its effectiveness. It may be necessary to increase the dose of EQUETRO if used concomitantly with a CYP3A4 inducer. Such drugs include the following:

Aminophylline, cisplatin, doxorubicin, felbamate, phosphenytoin, methsuximide, phenobarbital, phenytoin, primidone, rifampinand theophylline.

7.2 Pharmacokinetic Effectsof EQUETRO on other Drugs

EQUETRO is a potent inducer of hepatic 3A4 and is also known to be an inducer of CYP1A2, 2B6, 2C9/19 and may therefore reduce plasma concentrations of co-medications mainly metabolized by CYP 1A2, 2B6, 2C9/19 and 3A4, through induction of their metabolism. When used concomitantly with EQUETRO, monitoring of concentrations or dosage adjustment of these agents may be necessary.

EQUETRO decreases the concentrations of the following drugs through induction of their metabolism:

Hormonal Contraceptives (CYP3A4 Substrates)

EQUETRO is a strong inducer of CYP3A4. EQUETRO can increase the metabolism of certain hormonal contraceptives (through CYP3A4 induction) such as oral and subdermal implant contraceptives, leading to significantly lower plasma concentrations of hormones. This can cause contraceptive failure or breakthrough bleeding. Consider alternatives to oral and subdermal implant contraceptives that are significantly affected by induction of CYP3A4; or consider alternatives to EQUETRO [see Warnings and Precautions (5.5) and Use in Specific Populations (8.3)].

Delavirdine and other Non-Nucleoside Reverse Transcriptase Inhibitors (CYP3A4 Substrates)

Through induction of CYP3A4, EQUETRO increases the metabolism of delavirdine and certain non-nucleoside reverse transcriptase inhibitors and significantly reduces the plasma concentrations of these drugs. This can cause inadequate antiviral activity, loss of virologic response, and possible resistance to delavirdine or other non-nucleoside reverse transcriptase inhibitors. Therefore, the use of EQUETRO with these non-nucleoside reverse transcriptase inhibitors is contraindicated [see Contraindications (4) and Warnings and Precautions (5.9)].

Nefazodone (CYP3A4 Substrate)

The use of EQUETRO is contraindicated with the use of nefazodone because the concomitant use may result in insufficient plasma concentrations of nefazodone and its active metabolite to achieve a therapeutic effect of nefazodone.

Warfarin (CYP1A2 and CYP3A4 Substrate)

Through induction of CYP1A2 and CYP3A4, EQUETRO decreases the concentration of warfarin and decreases its anticoagulant effectiveness.

Aripiprazole

When carbamazepine is added to aripiprazole, the aripiprazole dose should be doubled. Additional dose increases should be based on clinical evaluation. If carbamazepine is later withdrawn, the aripiprazole dose should be reduced.

Tacrolimus

When carbamazepine is used with tacrolimus, monitoring of tacrolimus blood concentrations and appropriate dosage adjustments are recommended.

Temsirolimus

The use of concomitant strong CYP3A4 inducers such as carbamazepine should be avoided with temsirolimus. If patients must be coadministered carbamazepine with temsirolimus, an adjustment of temsirolimus dosage should be considered.

Lapatinib

The use of carbamazepine with lapatinib should generally be avoided. If carbamazepine is started in a patient already taking lapatinib, the dose of lapatinib should be gradually titrated up. If carbamazepine is discontinued, the lapatinib dose should be reduced.

HIV Protease Inhibitors

Due to strong induction of CYP3A4 caused by carbamazepine, use of EQUETRO with HIV protease inhibitors is not recommended.

Other CYP1A2 and CYP3A4 Substrates

EQUETRO induces CYP1A2 and CYP3A4, leading to decreased concentrations of drugs metabolized by CYP3A4 or CYP1A2. It may be necessary to increase the doses of such drugs when used concomitantly with EQUETRO. Drugs metabolized by CYP3A4 or CYP1A2 include the following:

Acetaminophen, albendazole, alprazolam, aprepitant, buprenorphone, bupropion, buspirone, citalopram, clobazam, clonazepam, clozapine, cyclosporin, delavirdine, desipramine, diazepam, dicumarol, dihydropyridine calcium channel blockers (e.g., felodipine), doxycycline, ethosuximide, everolimus, felbamate, glucocorticoids, haloperidol, imatinib, itraconazole, lamotrigine, levothyroxine, lorazepam, methadone, methsuxamide, mianserin, midazolam, mirtazapine, nefazodone, olanzapine, oral and other hormonal contraceptives, oxcarbazepine, paliperidone, phenytoin, praziquantel, quetiapine, risperidone, sertraline, sirolimus, tadalafil, theophylline, topiramate, tiagabine, tramadol, triazolam, tricyclic antidepressants (e.g., imipramine, amitriptyline, nortriptyline), trazodone, valproate, warfarin, ziprasidone, and zonisamide.

EQUETRO increases the plasma levels of the followingdrugsby inhibition of their metabolism:

Clomipramine, Phenytoin, and Primidone

EQUETRO can increase the concentrations of clomipramine, phenytoin, and primidone. If a patient has been titrated to a stable dosage on one of these agents in this category, and then begins treatment with EQUETRO, it may be necessary to decrease the dose of these drugs.

Phenytoin

Phenytoin levels have been reported to increase or decrease in the presence of carbamazepine. There are multiple pharmacokinetic mechanisms for changes in phenytoin levels when used concomitantly with EQUETRO. Monitor phenytoin serum levels carefully when used concomitantly with EQUETRO.

Cyclophosphamide

Cyclophosphamide is an inactive prodrug and is converted to its active metabolite in part by CYP3A. The rate of metabolism and the leukopenic activity of cyclophosphamide are reportedly increased by chronic co-administration of CYP3A4 inducers. There is a potential for increased cyclophosphamide toxicity when coadministered with carbamazepine.

7.3 Pharmacodynamic Drug Interactions

Monoamine Oxidase Inhibitors

Concomitant treatment with EQUETRO is contraindicated during use of an MAOI or within 14 days after discontinuing an MAOI. Concomitant use can cause serotonin syndrome.

Lithium

Concomitant administration of EQUETRO and lithium can increase the risk of neurotoxic adverse reactions. Consider reducing the dose of lithium or EQUETRO when using these drugs concomitantly.

Isoniazid

Concomitant use of carbamazepine and isoniazid has been reported to increase isoniazid-induced hepatotoxicity.

CNS Depressants

The concomitant use of EQUETRO and other CNS depressants can increase the risk of respiratory depression, profound sedation, hypotension, and syncope. CNS depressants include: alcohol, opioid analgesics, benzodiazepines, tricyclic antidepressants, sedative/hypnotics, anticonvulsants, antipsychotics, antihistamines, anticholinergics, alpha and beta blockers, general anesthetics, muscle relaxants, and illicit CNS depressants. Consider reducing the dose of CNS depressants or EQUETRO when using these drugs concomitantly.

Chloroquine and Mefloquine

The anti-malarial drugs chloroquine and mefloquine can antagonize the activity of EQUETRO.

Neuromuscular Blocking Agents

Resistance to the neuromuscular blocking action of the nondepolarizing neuromuscular blocking agents pancuronium, vecuronium, rocuronium and cisatracurium has occurred in patients chronically administered carbamazepine. Whether or not carbamazepine has the same effect on other nondepolarizing agents is unknown. Patients should be monitored closely for more rapid recovery from neuromuscular blockade than expected, and infusion rate requirements may be higher.

8 USE IN SPECIFIC POPULATIONS

8.1 Pregnancy

Pregnancy Exposure Registry

There is a pregnancy exposure registry that monitors pregnancy outcomes in women exposed to antiepileptic drugs (AEDs), such as EQUETRO, during pregnancy. Healthcare providers are encouraged to recommend that pregnant patients taking EQUETRO enroll in the North American Antiepileptic Drug (NAAED) Pregnancy Registry by calling 1-888-233-2334 or online at http://www.aedpregnancyregistry.org/.

Risk Summary

EQUETRO can cause fetal harm when administered to a pregnantfemale [see Warnings and Precautions (5.5)]. Pregnancy registry and epidemiological data suggest a potential association between the use of carbamazepine during pregnancy and major congenital malformations, including neural tube defects and malformations involving other body systems (e.g., craniofacial defects and cardiovascular malformations). The available data are insufficient to identify an association with carbamazepine use and miscarriage (see Data).There are risks to the mother and fetus associated with untreated bipolar I disorder or epilepsy and with exposure to carbamazepine during pregnancy (see Clinical Considerations).In animal studies, administration of carbamazepine at clinically relevant doses during pregnancy resulted in developmental toxicity, including increased incidences of fetal malformation. Advise pregnant females of the potential risk of major congenital malformations with use of EQUETRO during pregnancy. Assess the risk and benefits of EQUETRO and discuss with the patient to determine if an alternative treatment should be considered during pregnancy.

Dietary folic acid supplementation both prior to conception and during pregnancy should be recommended for patients using carbamazepine. However, it is not known whether the risk of neural tube defects in the offspring of women receiving carbamazepine is reduced by folic supplementation. Evidence suggests that folic acid supplementation prior to conception and during the first trimester of pregnancy decreases the risk for congenital neural tube defects in the general population.

All pregnancies have a background risk of birth defect, loss, or other adverse outcomes. In the U.S. general population, the estimated background risk of major birth defects and miscarriage in clinically recognized pregnancies is 2 to 4% and 15 to 20%, respectively. The background risk of major birth defects and miscarriage for the indicated population is unknown.

Clinical Considerations

Disease-associated Maternal and/or Embryofetal Risk

There are risks to the mother from untreated bipolar I disorder, including increased risk of relapse, hospitalization, and suicide. Bipolar I disorder is associated with increased adverse perinatal outcomes, including preterm birth. It is not known if this is a direct result of the illness or other comorbid factors.

Epilepsy, with or without exposure to antiepileptic drugs, has been associated with several adverse outcomes during pregnancy, including preeclampsia, preterm labor, antepartum and postpartum hemorrhage, placental abruption, poor fetal growth, prematurity, fetal death, and maternal mortality. The risk of maternal or fetal injury may be greatest for patients with untreated or poorly controlled convulsive seizures. Females with epilepsy should not discontinue carbamazepine abruptly due to the risk of status epilepticus and less severe seizures which may be life-threatening [see Warnings and Precautions (5.6)].

Fetal/Neonatal Adverse Reactions

There have been a few cases of neonatal seizures and/or respiratory depression associated with maternal carbamazepine and other concomitant anticonvulsant drug use. A few cases of neonatal vomiting, diarrhea, and/or decreased feeding have also been reported in association with maternal carbamazepine use. These symptoms may represent a neonatal withdrawal syndrome. Published studies have demonstrated that carbamazepine crosses the placenta.

Data

Human Data

Pregnancy registry and epidemiological data suggest a potential association between the use of carbamazepine during pregnancy and major congenital malformations, including neural tube defects and malformations involving other body systems (e.g., craniofacial defects and cardiovascular malformations). These available data suggest that, compared with monotherapy, there may be a higher prevalence of teratogenic effects associated with the use of anticonvulsants in combination therapy.

The North American Antiepileptic Drug (NAAED) Pregnancy Registry has reported a rate of major congenital malformations of 3.0% (95% CI: 2.1, 4.2) among pregnant females exposed to carbamazepine monotherapy (n=1,033) during the first trimester with a relative risk of 2.7 (95% CI: 1.0, 7.0) compared to pregnant females not taking an epileptic drug. The European Registry of Antiepileptic Drugs and Pregnancy (EURAP), a large international pregnancy registry focused outside of North America, reported major birth defects in 5.5% (95% CI: 4.5, 6.6) of 1,957 exposures to carbamazepine monotherapy in the first trimester. The UK Epilepsy and Pregnancy Register reported major birth defects in 2.6% (95% CI: 1.9-3.5) of 1,657 exposures to carbamazepine during the first three months of pregnancy.

Animal Data

In studies in which pregnant rats were administered carbamazepine orally during organogenesis, dose-related increases in the rates of fetal structural abnormalities (craniofacial, skeletal, cardiac, and urogenital defects), intrauterine growth retardation, and embryofetal death occurred at clinically relevant doses.

8.2 Lactation

Carbamazepine and its epoxide metabolite are present in human milk. Most infants with reported exposure to carbamazepine through human milk have not had adverse reactions; however, there are a few reported cases of hepatitis, regurgitations, poor weight gain, and vomiting in breastfed infants of females taking carbamazepine. There are no data on the effects of carbamazepine on milk production. The developmental and health benefits of breastfeeding should be considered along with the mother’s clinical need for EQUETRO and any potential adverse effects on the breastfed child from EQUETRO or from the underlying maternal condition.

8.3 Females and Males of Reproductive Potential

In females currently on EQUETRO who may become pregnant, assess the risks and benefits of continuing on EQUETRO and discuss with the patient if an alternative treatment should be considered. Dietary folic acid supplementation both prior to conception and during pregnancy should be recommended for patients using carbamazepine [see Warnings and Precautions (5.5), Use in Specific Populations (8.1)].

Contraception

EQUETRO can increase metabolism of certain hormonal contraceptives (through CYP3A4 induction) such as oral and subdermal implant contraceptives, leading to significant lower plasma concentrations of hormones. This can cause contraceptive failure or breakthrough bleeding. Consider alternatives to oral and subdermal implant contraceptives that are significantly affected by induction of CYP3A4; or consider alternatives to EQUETRO [see Drug Interactions (7.2)].

Infertility

Based on human and animal findings, EQUETRO may impair male fertility. Published clinical studies have reported a reduction in semen quality in males of reproductive potential with epilepsy that were treated with carbamazepine [see Nonclinical Toxicology (13.1)].

8.4 Pediatric Use

Bipolar Disorder and Pain of Trigeminal Neuralgia

The safety and effectiveness of EQUETRO have not been established in pediatric patients.

8.5 Geriatric Use

Clinical studies of EQUETRO did not include sufficient numbers of subjects age 65 and over to determine whether they respond differently from younger subjects. Other reported clinical experience has not identified differences in responses between the elderly and younger patients. In general, dose selection for an elderly patient should be cautious, usually starting at the low end of the dosing range, reflecting the greater frequency of decreased hepatic, renal, or cardiac function, and of concomitant disease or other drug therapy.

10 OVERDOSAGE

10.1 Human Experience

Lowest known lethal dose of carbamazepine: adults, greater than 60 grams (39-year-old man). Highest known doses survived: adults, 30 grams (31-year-old woman); children, 10 grams (6-year-old boy); small children, 5 grams (3-year-old girl).

Signs and Symptoms:The first signs and symptoms of carbamazepine overdose appear after 1 to 3 hours. Neuromuscular disturbances are the most prominent. Cardiovascular disorders are generally milder, and severe cardiac complications occur only when very high doses (greater than 60 grams) have been ingested.

Respiration:Irregular breathing, respiratory depression.

Cardiovascular System:Tachycardia, hypotension or hypertension, shock, conduction disorders.

Nervous System and Muscles:Impairment of consciousness ranging in severity to deep coma. Convulsions, especially in small children. Motor restlessness, muscular twitching, tremor, athetoid movements, opisthotonos, ataxia, drowsiness, dizziness, mydriasis, nystagmus, adiadochokinesia, ballism, psychomotor disturbances, dysmetria. Initial hyperreflexia, followed by hyporeflexia.

Gastrointestinal Tract:Nausea, vomiting.

Kidneys and Bladder:Anuria or oliguria, urinary retention.

Laboratory Findings:Isolated instances of overdosage have included leukocytosis, reduced leukocyte count, glycosuria, and acetonuria. ECG may show dysrhythmias.

Combined Poisoning:When alcohol, tricyclic antidepressants, barbiturates, or hydantoins are taken at the same time, the signs and symptoms of acute poisoning with carbamazepine may be aggravated or modified.

10.2 Management of Overdosage

For the most up to date information on management of EQUETRO overdose, contact the certified poison center for your area by calling 1-800-222-1222 (or at www.poison.org). In case of an overdose, provide supportive care, including close medical supervision and monitoring. Treatment should consist of those general measures employed in the management of overdosage with any drug. Consider the possibility of multiple drug overdose. Ensure an adequate airway, oxygenation, and ventilation. Monitor cardiac rhythm and vital signs. Use supportive and symptomatic measures.

11 DESCRIPTION

EQUETRO (carbamazepine) is a mood stabilizer available for oral administration as 100 mg, 200 mg, and 300 mg extended-release capsules of carbamazepine, USP. Carbamazepine is a white to off-white powder, practically insoluble in water and soluble in alcohol and in acetone. Its molecular weight is 236.27. The chemical name of carbamazepine is 5H-dibenz[b,f]azepine-5-carboxamide, and the structural formula is:

EQUETRO®is a multi-component capsule formulation consisting of three different types of beads: immediate-release beads, extended-release beads, and enteric-release beads. The three bead types are combined in a specific ratio to provide twice-daily dosing of EQUETRO®.

Inactive ingredients:citric acid, colloidal silicon dioxide, lactose monohydrate, microcrystalline cellulose, polyethylene glycol, povidone, sodium lauryl sulfate, talc, triethyl citrate, and other ingredients.

The 100 mg capsule shells contain gelatin-NF, FD&C Blue #2, Yellow Iron Oxide, and Titanium Dioxide, and are imprinted with white ink; the 200 mg capsule shells contain gelatin-NF, Yellow Iron Oxide, FD&C Blue #2, and Titanium Dioxide, and are imprinted with white ink; and the 300 mg capsule shells contain gelatin-NF, FD&C Blue #2, Yellow Iron Oxide, and Titanium Dioxide, and are imprinted with white ink.

12 CLINICAL PHARMACOLOGY

12.1 Mechanism of Action

The mechanism of action of carbamazepine in the treatment of acute manic or mixed episodes associated with bipolar disorder is unclear.

12.3 Pharmacokinetics

Carbamazepine (CBZ)

Absorption:Following a single 200 mg oral extended-release dose of carbamazepine, peak plasma concentration was 1.9 ± 0.3 mcg/mL and the time to reach the peak was 19 ± 7 hours. Following repeat dose administration (800 mg every 12 hours), the peak levels were 11.0 ± 2.5 mcg/mL and the time to reach the peak was 5.9 ± 1.8 hours. The pharmacokinetics of extended-release carbamazepine is linear over the single dose range of 200–800 mg.

Carbamazepine is 76% bound to plasma proteins. Carbamazepine is primarily metabolized in the liver. Cytochrome P450 3A4 was identified as the major isoform responsible for the formation of carbamazepine-10,11-epoxide. Since carbamazepine induces its own metabolism, the half-life is also variable. The average half-life ranged from 35 to 40 hours following a single extended-release dose of carbamazepine and from 12 to 17 hours following repeated dosing. The apparent oral clearance was 25 ± 5 mL/min following a single dose and 80 ± 30 mL/min following multiple dosing.

Carbamazepine-10,11-epoxide (CBZ-E):Carbamazepine-10,11-epoxide is considered to be an active metabolite of carbamazepine. Following a single 200 mg oral extended-release dose of carbamazepine, the peak plasma concentration of carbamazepine-10,11-epoxide was 0.11 ± 0.012 mcg/mL and the time to reach the peak was 36 ± 6 hours. Following chronic administration of an extended-release dose of carbamazepine (800 mg every 12 hours), the peak levels of carbamazepine-10,11-epoxide were 2.2 ± 0.9 mcg/mL and the time to reach the peak was 14 ± 8 hours. The plasma half-life of carbamazepine-10,11-epoxide following administration of carbamazepine is 34 ± 9 hours. Following a single oral dose of extended-release carbamazepine (200–800 mg) the AUC and Cmaxof carbamazepine-10,11-epoxide were less than 10% of carbamazepine. Following multiple dosing of extended-release carbamazepine (800–1600 mg daily for 14 days), the AUC and Cmaxof carbamazepine-10,11-epoxide were dose-related, ranging from 15.7 mcg.hr/mL and 1.5 mcg/mL at 800 mg/day to 32.6 mcg.hr/mL and 3.2 mcg/mL at 1600 mg/day, respectively, and were less than 30% those of carbamazepine. Carbamazepine-10,11-epoxide is 50% bound to plasma proteins.

Food Effect:A high-fat meal diet increased the rate of absorption of a single 400 mg dose (mean Tmaxwas reduced from 24 hours, in the fasting state, to 14 hours, and Cmaxincreased from 3.2 to 4.3 mcg/mL) but not the extent (AUC) of absorption. The elimination half-life remained unchanged between fed and fasting state. The multiple-dose study conducted in the fed state showed that the steady-state Cmaxvalues were within the therapeutic concentration range. The pharmacokinetic profile of extended-release carbamazepine was similar when given by sprinkling the beads over applesauce compared to the intact capsule administered in the fasted state.

Elimination:After oral administration of^14C-carbamazepine, 72% of the administered radioactivity was found in the urine and 28% was found in the feces. This urinary radioactivity was composed largely of hydroxylated and conjugated metabolites, with only 3% of unchanged carbamazepine.

Metabolism:In vitro data indicate carbamazepine is metabolized mainly by cytochrome P450 (CYP) 3A4 to the active carbamazepine-10,11-epoxide, which is further metabolized to the transdiol by epoxide hydrolase. Human microsomal epoxide hydrolase has been identified as the enzyme responsible for the formation of the 10,11-transdiol derivative from carbamazepine-10,11-epoxide.

Renal Impairment:The effect of renal impairment on the pharmacokinetics of carbamazepine is not known.

Hepatic Impairment:The effect of hepatic impairment on the pharmacokinetics of carbamazepine is not known. Consider reducing the dosage in patients with hepatic impairment.

Effect of Age:Carbamazepine is more rapidly metabolized to carbamazepine-10,11-epoxide in young children than in adults. In children below the age of 15, there is an inverse relationship between CBZ-E/CBZ ratio and increasing age. The safety and effectiveness of EQUETRO have not been established in pediatric patients for indications other than Epilepsy [see Indications and Usage (1.3)].

Effect of Gender:No difference in the mean AUC and Cmaxof carbamazepine and carbamazepine-10,11-epoxide was found between males and females.

13 NONCLINICAL TOXICOLOGY

13.1 Carcinogenesis, Mutagenesis, and Impairment of Fertility

Carcinogenicity

Oral administration of carbamazepine to rats for 2 years at doses of 25, 75, and 250 mg/kg/day resulted in a dose-related increase in the incidence of hepatocellular tumors (females) and of benign interstitial cell adenomas in the testes.

Mutagenicity

Carbamazepine was negative in in vitro bacterial and mammalian genotoxicity.

Impairment of Fertility

The effects of carbamazepine on male and female fertility have not been adequately studied in animals. However, testicular atrophy and/or aspermatogenesis were observed in rats with repeat oral administration of carbamazepine at clinically relevant doses.

14 CLINICAL STUDIES

14.1 Bipolar I Disorder (Acute Manic or Mixed Episodes)

The efficacy of EQUETRO in the acute treatment of manic or mixed symptoms associated with bipolar I disorder was established in two 3-week, multicenter, randomized, double-blind, placebo-controlled, flexible-dose studies (Studies 1 and 2) in adult patients who met the DSM-IV criteria for bipolar I disorder, manic or mixed episode. In both studies, patients must have had a history of at least one previous manic or mixed episode. They must have had a Young Mania Rating Scale (YMRS) baseline score of at least 20. The YMRS is an 11-item instrument, ranging from 0 to 60 (greater score indicates a more severe manic disorder) that measures symptoms associated with a manic state: elevated mood, increased motor activity/energy, sexual interest, sleep, irritability, speech, language-thought disorder, content, disruptive/aggressive behavior, appearance, and insight.

In Studies 1 and 2, patients were hospitalized for at least one week. They received placebo during a 5-day lead-in period and subsequently were randomized to receive placebo or EQUETRO, initially at a dose of 200 mg twice daily (400 mg per day). If tolerated, the total daily dose could be increased by 200 mg once daily to a maximum dose of 800 mg twice daily (1600 mg/day). The mean EQUETRO dose during the last week was 952 mg/day in Study 1 and 726 mg/day in Study 2.

Patients were permitted to receive lorazepam for agitation or insomnia up to 6 mg/day during the placebo-lead in period, up to 4 mg/day during the first week of controlled treatment, and up to 2 mg/day during the second week of treatment; no lorazepam was permitted during the third week of treatment. They were permitted to continue their routine psychotherapy. Patients were not allowed to use antipsychotics, lithium, antidepressants, or sedatives/hypnotics (other than lorazepam) during the studies. There were no significant differences in lorazepam use between the EQUETRO and placebo groups in both studies.

In Studies 1 and 2, the primary endpoint was the mean change from baseline in the YMRS total score at Day 21. In both studies, treatment with EQUETRO was statistically significantly superior to placebo, as measured by the mean decrease in YMRS score at Day 21 (Table 3).

The key secondary efficacy endpoint in both trials was the change in Clinical Global Impression-Severity (CGI-S) Scale score. The CGI-S an investigator-rated global assessment of symptom severity that is scored on a 7-point scale (1 = normal, not ill); (7 = severely ill). In both studies, there was a statistically significant decrease from baseline in the mean CGI-S score at Day 21, compared to placebo (Table 3).

Table 3. Efficacy Results in the 2 Trials in Patients with Bipolar I Disorder – Change in mean YMRS score from baseline to Week 3 and change in mean CGI-S from baseline to Week 3
 | Study 1 |  | Study 2
 | EQUETRO (n=94) | Placebo (n=98) | EQUETRO (n=120) | Placebo (n=115)
Young Mania Rating Scale (YMRS)
Baseline YMRS | 26.6 | 27.3 | 28.5 | 27.9
Week 3 YMRS | 17.9 | 22.1 | 13.4 | 20.8
LS mean change | -7.8 | -4.8 | -14.8 | -7.0
LS mean difference from placebo* | -3.5 | ─ | -8.0 | ─
p-value | P= 0.033 |  | < 0.0001
Clinical Global Impression-Severity Scale (CGI-S)
Baseline CGI-S | 4.4 | 4.4 | 4.5 | 4.5
Week 3 CGI-S | 3.7 | 4.1 | 3 | 3.9
Change from Baseline at Week 3 | -0.7 | -0.3 | -1.5 | -0.6
Difference (p-value) | -0.4 (0.025) | ─ | -0.9 (< 0.0001) | ─

* Least squares mean for the difference defined as the change from baseline at Week 3 in the EQUETRO group minus that in the placebo group.

14.2 Epilepsy

Evidence supporting efficacy of carbamazepine as an anticonvulsant was derived from active drug-controlled studies that enrolled patients with the following seizure types:

1. Partial seizures with complex symptomatology (psychomotor, temporal lobe). Patients with these seizures appear to show greater improvements than those with other types.
2. Generalized tonic-clonic seizures (grand mal).
3. Mixed seizure patterns which include the above, or other partial or generalized seizures.

Absence seizures (petit mal) do not appear to be controlled by carbamazepine.

16 HOW SUPPLIED/STORAGE AND HANDLING

16.1 How Supplied

EQUETRO (carbamazepine) extended-release capsules are supplied in three dosage strengths.

- 100 mg — Two-piece hard gelatin capsule yellow opaque cap with bluish green opaque body printed with SPD417 on one end and SPD417 and 100 mg on the other in white ink: Supplied in bottles of 120
  NDC 30698-419-12

- 200 mg — Two-piece hard gelatin capsule yellow opaque cap with blue opaque body printed with SPD417 on one end and SPD417 and 200 mg on the other in white ink: Supplied in bottles of 120
  NDC 30698-421-12

- 300 mg — Two-piece hard gelatin capsule yellow opaque cap with blue body printed with SPD417 on one end and SPD417 and 300 mg on the other in white ink: Supplied in bottles of 120
  NDC 30698-423-12

16.2 Storage

Store at 25° C (77°F); excursions permitted to 15°–30° C (59°–86° F) [see USP controlled room temperature].

Protect from light and moisture.

17 PATIENT COUNSELING INFORMATION

Advise the patient to read the FDA-approved patient labeling (Medication Guide).

- Serious Dermatologic Reactions
  Inform patients and caregivers about the risk of potentially fatal, serious skin reactions and the signs and symptoms that may signal a serious skin reaction. Instruct patients to consult with their healthcare provider immediately if a skin reaction occurs during treatment with EQUETRO [see Warnings and Precautions (5.1)].
- Agranulocytosis and Aplastic Anemia
  Inform patients and caregivers about the risk of potentially fatal agranulocytosis and aplastic anemia and the signs and symptoms that may signal these reactions. Instruct them to contact their healthcare provider immediately if symptoms occur [see Warnings and Precautions (5.2)].
- Drug Reaction with Eosinophilia and Systemic Symptoms
  Inform patients of the early toxic signs and symptoms of a potential hematologic, dermatologic, hypersensitivity, or hepatic reactions. Advise patients that these signs and symptoms may signal a serious reaction and to report any occurrence immediately to their healthcare provider [see Warnings and Precautions (5.3)].
- Suicidal Ideation and Behavior
  Counsel patients, their caregivers, and families that AEDs, including EQUETRO, may increase the risk of suicidal thinking and behavior and advise them of the need to be alert for the emergence or worsening of symptoms of depression, any unusual changes in mood or behavior, or the emergence of suicidal thoughts, behavior, or thoughts about self-harm. Instruct patients, caregivers and families to report behaviors of concern immediately to healthcare providers [see Warnings and Precautions (5.4)].
- Abrupt Discontinuation and Risk of Seizure
  Inform patients that abrupt discontinuation of EQUETRO can cause seizures or an increase in seizure frequency. Advise patients that the drug should be tapered when discontinued [see Warningsand Precautions (5.6)].
- Hyponatremia
  Advise patients that EQUETRO may reduce serum sodium concentrations especially if they are taking other medications that can lower sodium. Advise patients to report symptoms of low sodium like nausea, tiredness, lack of energy, confusion, seizures, or more frequent or more severe seizures [see Warnings and Precautions (5.7)].
- Potential for Cognitive and Motor Impairment
  Advise patients not to drive or operate machinery until they have gained sufficient experience on EQUETRO to gauge whether it adversely affects their ability to drive or operate machinery.
  Advise patients to exercise caution if alcohol is taken in combination with EQUETRO therapy, due to a possible additive sedative effect [see Warnings and Precautions (5.8)].
- Concomitant Use with other Carbamazepine Products
  Inform patients that EQUETRO contains carbamazepine and should not be used in combination with any other medications containing carbamazepine.
- Embryofetal Toxicity
  EQUETRO may cause fetal harm. Advise females of reproductive potential to inform their healthcare provider of a known or suspected pregnancy. [see Warning and Precautions (5.5) and Use in Specific Populations (8.1)].
- Pregnancy
  Advise patients that there is a pregnancy registry that monitors pregnancy outcomes in women exposed to EQUETRO during pregnancy [see Use in Specific Populations (8.1)].
- Decreased Effectiveness of Hormonal Contraceptives
  Inform patients that EQUETRO can significantly decrease the effectiveness of hormonal contraceptives, such as oral contraceptives and subdermal implants. This can cause contraceptive failure or breakthrough bleeding [see Drug Interactions (7.2) and Use in Specific Populations (8.3)].
- Infertility
  Advise males of reproductive potential that EQUETRO may impair fertility [see Use in Specific Populations (8.3)].

Manufactured for and Distributed by:
Validus Pharmaceuticals LLC
Parsippany, NJ 07054
info@validuspharma.com
http://www.equetro.com
1-866-982-5438

Product of India

© 2022 Validus Pharmaceuticals LLC

60079-04 October 2022

Medication Guide

EQUETRO (ē-kwĕ-trō)

(carbamazepine)

Extended-Release Capsules

Read this Medication Guide before you start taking EQUETRO and each time you get a refill. There may be new information. This information does not take the place of talking to your healthcare provider about your medical condition or treatment.

What is the most important information I should know about EQUETRO?

Do not stop taking EQUETRO without first talking to your healthcare provider.

Stopping EQUETRO suddenly can cause serious problems.

If you have any of the problems listed below call your healthcare provider right away.

EQUETRO can cause serious side effects, including:

1. EQUETRO may cause rare but serious rashes that may lead to death. These serious skin reactions are more likely to happen within the first four months after you start taking EQUETRO, but may occur at later times. These reactions can happen to anyone, but are more likely in people of Asian descent. If you are of Asian descent, you may need a genetic blood test before you take EQUETRO to see if you are at higher risk for serious skin reactions with this medicine. Symptoms may include:

- skin rash
- hives
- sores in your mouth
- blistering or peeling of the skin

2. EQUETRO may cause rare but serious blood problems. Symptoms may include:

- fever
- shortness of breath
- fatigue
- easy bruising
- red or purple spots on your body
- unusual bleeding such as bleeding gums, nose bleeds, or heavy menstrual bleeding
- swollen glands and sore throat

3. EQUETRO may cause a serious or life-threatening allergic reaction that may affect your skin or other parts of your body such as your liver or blood cells. You may or may not have rash with these types of reactions. Call a healthcare provider right away if you have any of the following symptoms:

- skin rash
- hives
- fever
- swollen glands that do not go away
- swelling of your lips or tongue
- yellowing of your skin or eyes
- unusual bruising or bleeding
- severe fatigue or weakness
- unexpected, severe muscle pain
- frequent infections

These symptoms may be the first signs of a serious reaction. A healthcare provider should examine you to decide if you should continue taking EQUETRO.

4. EQUETRO may cause suicidal thoughts or actions in a very small number of people, about 1 in 500.

Call your healthcare provider right away if you have any of these symptoms, especially if they are new, worse, or worry you:

- thoughts about suicide or dying
- attempts to commit suicide
- new or worse depression
- new or worse anxiety
- feeling agitated or restless
- panic attacks
- trouble sleeping (insomnia)
- new or worse irritability
- acting aggressive, being angry, or violent
- acting on dangerous impulses
- an extreme increase in activity or talking (mania)
- other unusual changes in behavior or mood

How can I watch for early symptoms of suicidal thoughts and actions?

- Pay attention to any changes, especially sudden changes, in mood, behaviors, thoughts, or feelings.
- Keep all follow-up visits with your healthcare provider as scheduled.

Call your healthcare provider between visits as needed, especially if you are worried about symptoms.

Do not stop EQUETRO without first talking to a healthcare provider.

Stopping EQUETRO suddenly can cause serious problems. You should talk to your healthcare provider before stopping.

Suicidal thoughts or actions can be caused by things other than medicines. If you have suicidal thoughts or actions, your healthcare provider may check for other causes.

What is EQUETRO?

EQUETRO is a prescription medicine used to treat people with:

- acute manic or mixed episodes that happen with Bipolar I Disorder
- certain types of nerve pain (trigeminal neuralgia and glossopharyngeal neuralgia)
- certain types of seizures (partial, tonic-clonic, mixed)

EQUETRO is not a regular pain medicine and should not be used for aches or pains.

EQUETRO should not be used to treat people with absence seizures (petit mal).

It is not known if EQUETRO is safe and effective in children and adolescents for the treatment of Bipolar I Disorder and nerve pain.

Who should not take EQUETRO?

Do not take EQUETRO if you:

- have a history of bone marrow depression.
- are allergic to carbamazepine or any of the ingredients in EQUETRO. See the end of this Medication Guide for a complete list of ingredients in EQUETRO.
- are allergic to medicines called tricyclic antidepressants (TCAs). Ask your healthcare provider or pharmacist for a list of these medicines if you are not sure.
- are taking delaviridine or other medicines called reverse transcriptase inhibitors. Ask your healthcare provider or pharmacist for a list of these medicines if you are not sure.
- have taken a medicine called a Monoamine Oxidase Inhibitor (MAOI) in the last 14 days. Ask your healthcare provider or pharmacist for a list of these medicines if you are not sure.
- are taking nefazodone.

What should I tell my healthcare provider before taking EQUETRO?

Before you take EQUETRO, tell your healthcare provider if you:

- have or have had suicidal thoughts or actions, depression or mood problems
- have or ever had heart problems
- have or ever had blood problems
- have or ever had liver problems
- have or ever had kidney problems
- have or ever had allergic reactions to medicines
- have or ever had increased pressure in your eye
- have any other medical conditions
- drink grapefruit juice or eat grapefruit
- use birth control. EQUETRO may make your birth control less effective. Tell your healthcare provider if your menstrual bleeding changes while you take birth control and EQUETRO.
- are pregnant or plan to become pregnant. EQUETRO may harm your unborn baby. Tell your healthcare provider right away if you become pregnant while taking EQUETRO. You and your healthcare provider will decide if you should take EQUETRO while you are pregnant.
  ○ If you become pregnant while taking EQUETRO, talk to your healthcare provider about registering with the North American Antiepileptic Drug (NAAED) Pregnancy Registry. You can register by calling 1-888-233-2334. For more information about the registry go to http://www.aedpregnancyregistry.org. The purpose of this registry is to collect information about the safety of antiepileptic drugs during pregnancy.
- are breastfeeding or plan to breastfeed. EQUETRO can pass into breast milk.
  ○ Talk to your healthcare provider about the best way to feed your baby while you take EQUETRO.

Tell your healthcare provider about all the medicines you take, including prescription and non-prescription medicines, vitamins, and herbal supplements.

Taking EQUETRO with certain other medicines may cause side effects or affect how well they work. Do not stop or start other medicines without talking to your healthcare provider.

Know the medicines you take. Keep a list of them and show it to your healthcare provider and pharmacist when you get a new medicine.

How should I take EQUETRO?

- Do not stop taking EQUETRO without first talking to your healthcare provider. Stopping EQUETRO suddenly can cause serious problems.
- Take EQUETRO exactly as prescribed. Your healthcare provider will tell you how much EQUETRO to take.
- Your healthcare provider may change your dose. Do not change your dose of EQUETRO without talking to your healthcare provider.
- Swallow EQUETRO capsules whole. Do not crush or chew.
  ○ If you cannot swallow EQUETRO capsules whole, you may open the EQUETRO capsules and sprinkle the beads over food such as a teaspoon of applesauce and swallow the mixture. Do not crush or chew the beads.
- Take EQUETRO with or without food.
- If you take too much EQUETRO, call your healthcare provider or local Poison Control Center right away.

What should I avoid while taking EQUETRO?

- Do not drink alcohol or take other drugs that make you sleepy or dizzy while taking EQUETRO until you talk to your healthcare provider. EQUETRO taken with alcohol or drugs that cause sleepiness or dizziness may make your sleepiness or dizziness worse.
- Do not drive, operate heavy machinery, or do other dangerous activities until you know how EQUETRO affects you. EQUETRO can slow your thinking and motor skills.

What are the possible side effects of EQUETRO?

See “What is the most important information I should know about EQUETRO?”

EQUETRO may cause other serious side effects, including:

- Seizure risk.Stopping EQUTERO suddenly may cause you to have a seizure. The risk of seizures may be higher in people who already have seizures. Do not stop taking EQUETRO without first talking with your healthcare provider.
- Low level of sodium in your blood (hyponatremia).Symptoms of hyponatremia may include:
  ○ headache
  ○ new seizures or an increased number of seizures
  ○ difficulty concentrating
  ○ memory problems
  ○ confusion
  ○ weakness
  ○ balance problems
- Problems with judgment, thinking, and movement.
- Liver problems.Symptoms of liver problems may include:
  ○ yellowing of your skin or the whites of your eyes
  ○ dark urine
  ○ pain on the right side of your stomach area (abdominal pain)
  ○ easy bruising
  ○ loss of appetite
  ○ nausea or vomiting

Get medical help right away if you have any of the symptoms listed above or listed in “What is the most important information I should know about EQUETRO?”

The most common side effects of EQUETRO include:

- dizziness
- drowsiness
- nausea
- vomiting
- problems with walking and coordination (unsteadiness)
- constipation
- itching
- dry mouth
- weakness
- blurred vision
- problems speaking

EQUETRO may cause fertility problems in males. This may affect your ability to father a child while you are taking EQUETRO. Talk to your healthcare provider if this is a concern for you.

These are not all the possible side effects of EQUETRO. For more information, ask your healthcare provider or pharmacist.

Tell your healthcare provider if you have any side effect that bothers you or that does not go away.

To report SUSPECTED ADVERSE REACTIONS, contact Validus Pharmaceuticals LLC at 1-866-982-5438 or FDA at 1-800-FDA-1088 orwww.fda.gov/medwatch.

How should I store EQUETRO?

- Store EQUETRO between 68^0F to 77^0F (20^0C to 25^0C).
- Keep EQUETRO capsules out of the light.
- Keep EQUETRO capsules dry.

Keep EQUETRO and all medicines out of the reach of children.

General Information about the safe and effective use of EQUETRO.

Medicines are sometimes prescribed for purposes other than those listed in a Medication Guide. Do not use EQUETRO for a condition for which it was not prescribed. Do not give EQUETRO to other people, even if they have the same symptoms that you have. It may harm them.

This Medication Guide summarizes the most important information about EQUETRO. If you would like more information, talk with your healthcare provider. You can ask your pharmacist or healthcare provider for information about EQUETRO that is written for health professionals.

For more information, go to www.EQUETRO.com or call 1-866-982-5438.

What are the ingredients in EQUETRO?

Active ingredient:carbamazepine

Inactive ingredients:citric acid, colloidal silicon dioxide, lactose monohydrate, microcrystalline cellulose, polyethylene glycol, povidone, sodium lauryl sulfate, talc, triethyl citrate, and other ingredients.

- 100mg capsule shell contains:gelatin-NF, FD&C Blue #2, Yellow Iron Oxide, and Titanium Dioxide, and are imprinted with white ink.
- 200mg capsule shell contains:gelatin-NF, Yellow Iron Oxide, FD&C Blue #2, and Titanium Dioxide, and are imprinted with white ink.
- 300mg capsule shell contains:gelatin-NF, FD&C Blue #2, Yellow Iron Oxide, and Titanium Dioxide, and are imprinted with white ink.

This Medication Guide has been approved by the U. S. Food and Drug Administration.

Manufactured for and Distributed by:
Validus Pharmaceuticals LLC
Parsippany, NJ 07054
info@validuspharma.com
http://www.equetro.com
1-866-982-5438

Product of India

© 2022 Validus Pharmaceuticals LLC

60080-04 October 2022

PACKAGE LABEL

PRINCIPAL DISPLAY PANEL

NDC 30698-419-12
Equetro® Extended - Release Capsules
(carbamazepine)
100 mg
120 Capsules
Rx Only

PACKAGE LABEL

PRINCIPAL DISPLAY PANEL

NDC 30698-421-12
Equetro® Extended - Release Capsules
(carbamazepine)
200 mg
120 Capsules
Rx Only

PACKAGE LABEL

PRINCIPAL DISPLAY PANEL

NDC 30698-423-12
Equetro® Extended - Release Capsules
(carbamazepine)
300 mg
120 Capsules
Rx Only